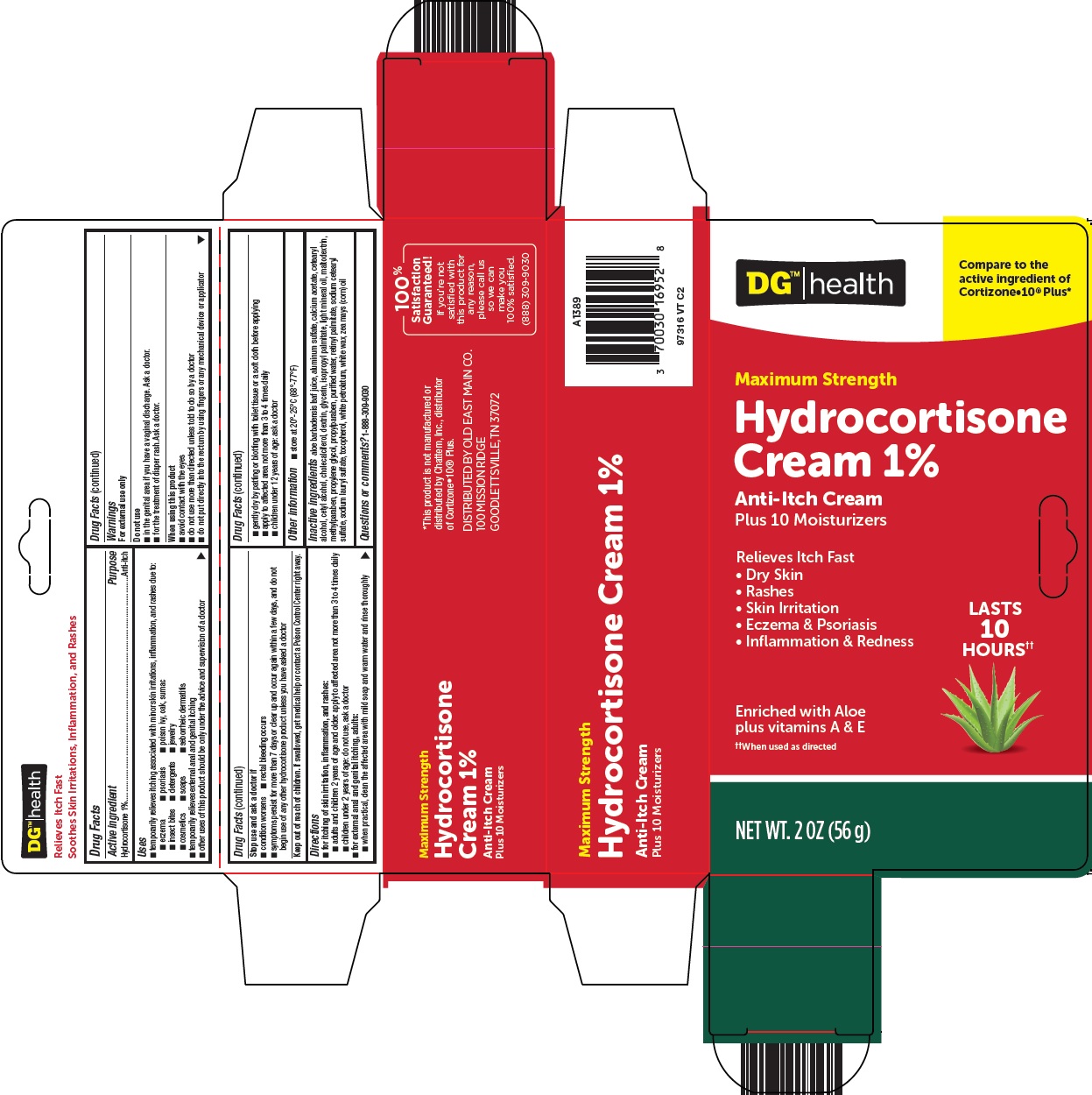 DRUG LABEL: DG health hydrocortisone
NDC: 55910-504 | Form: CREAM
Manufacturer: Dolgencorp, LLC
Category: otc | Type: HUMAN OTC DRUG LABEL
Date: 20241115

ACTIVE INGREDIENTS: HYDROCORTISONE 1 g/100 g
INACTIVE INGREDIENTS: ALOE VERA LEAF; ALUMINUM SULFATE; CALCIUM ACETATE; CETOSTEARYL ALCOHOL; CETYL ALCOHOL; CHOLECALCIFEROL; GLYCERIN; ISOPROPYL PALMITATE; LIGHT MINERAL OIL; MALTODEXTRIN; METHYLPARABEN; PROPYLENE GLYCOL; PROPYLPARABEN; WATER; VITAMIN A PALMITATE; SODIUM CETOSTEARYL SULFATE; SODIUM LAURYL SULFATE; TOCOPHEROL; PETROLATUM; WHITE WAX; CORN OIL; ICODEXTRIN

Dolgencorp, LLC Hydrocortisone Cream 1% Drug Facts

Active ingredient

Hydrocortisone 1%

Purpose

Anti-itch

Uses

- temporarily relieves itching associated with minor skin irritations, inflammation, and rashes due to:
- eczema
- psoriasis
- poison ivy, oak, sumac
- insect bites
- detergents
- jewelry
- cosmetics
- soaps
- seborrheic dermatitis
- temporarily relieves external anal and genital itching
- other uses of this product should be only under the advice and supervision of a doctor

Warnings

For external use only

Do not use

- in the genital area if you have a vaginal discharge. Ask a doctor.
- for the treatment of diaper rash. Ask a doctor.

When using this product

- avoid contact with the eyes
- do not use more than directed unless told to do so by a doctor
- do not put directly into the rectum by using fingers or any mechanical device or applicator

Stop use and ask a doctor if

- condition worsens
- symptoms persist for more than 7 days or clear up and occur again within a few days, and do not begin use of any other hydrocortisone product unless you have asked a doctor
- rectal bleeding occurs

Keep out of reach of children.

If swallowed, get medical help or contact a Poison Control Center right away.

Directions

- for itching of skin irritation, inflammation, and rashes:
- adults and children 2 years of age and older: apply to affected area not more than 3 to 4 times daily
- children under 2 years of age: do not use, ask a doctor
- for external anal and genital itching, adults:
- when practical, clean the affected area with mild soap and warm water and rinse thoroughly
- gently dry by patting or blotting with toilet tissue or a soft cloth before applying
- apply to affected area not more than 3 to 4 times daily
- children under 12 years of age: ask a doctor

Other information

- store at 20°-25°C (68°-77°F)

Inactive ingredients

aloe barbadensis leaf juice, aluminum sulfate, calcium acetate, cetearyl alcohol, cetyl alcohol, cholecalciferol, dextrin, glycerin, isopropyl palmitate, light mineral oil, maltodextrin, methylparaben, propylene glycol, propylparaben, purified water, retinyl palmitate, sodium cetearyl sulfate, sodium lauryl sulfate, tocopherol, white petrolatum, white wax, zea mays (corn) oil

Questions or comments?

1-888-309-9030

Principal Display Panel

DG™|health

Compare to the active ingredient of Cortizone•10® Plus

Maximum Strength

Hydrocortisone Cream 1%

Anti-Itch Cream

Plus 10 Moisturizers

Relieves Itch Fast

• Dry Skin

• Rashes

• Skin Irritation

• Eczema & Psoriasis

• Inflammation & Redness

LASTS 10 HOURS††

Enriched with Aloe

plus vitamins A & E

††When used as directed

NET WT. 2 OZ (56 g)